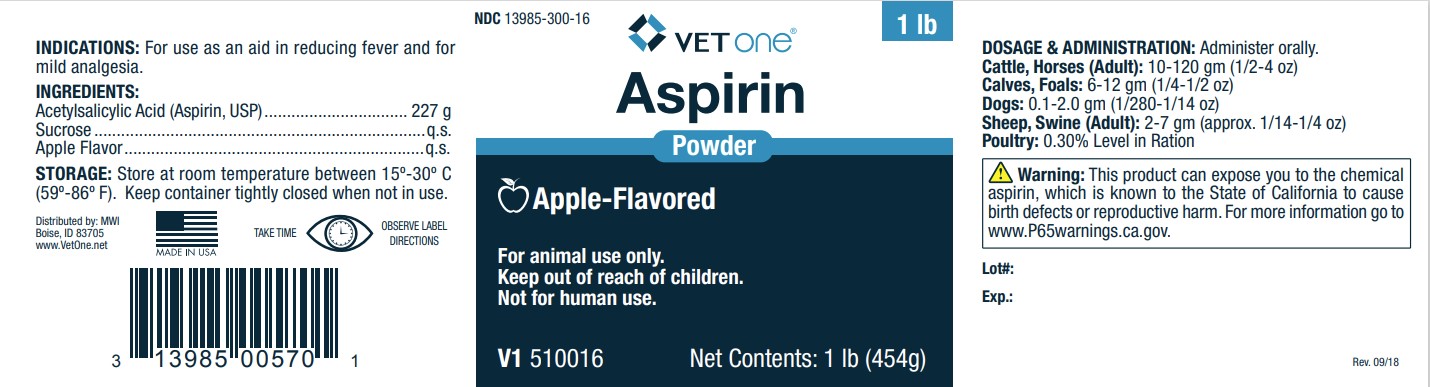 DRUG LABEL: Aspirin with Apple Flavoring
NDC: 13985-300 | Form: POWDER
Manufacturer: MWI Veterinary Supply, Inc.
Category: animal | Type: OTC ANIMAL DRUG LABEL
Date: 20240903

ACTIVE INGREDIENTS: ACETYLSALICYLSALICYLIC ACID 227 g/454 g
INACTIVE INGREDIENTS: SUCROSE

Active Ingredients:
Acetylsalicylic Acid (Aspirin USP) ........................................... 227 g

Inactive Ingredients:
Sucrose ..........................................................................q.s.
Apple Flavor...................................................................q.s.

STORAGE AND HANDLING

Store at room temperature between 15° and 30°C (59° - 86°F).
Keep container tightly closed when not in use.

Dosage and Administration: Administer Orally.
Cattle, Horses (Adult): 10-120 gm (1/2 - 4 oz)
Calves, Foals: 6-12 gm (1/4 - 1/2 oz)
Dogs: 0.1-2.0 gm (1/280 - 1/14 oz)
Sheep, Swine (Adult): 2-7 gm (1/14 - 1/4 oz)
Poultry: 0.30% Level in Ration

USER SAFETY WARNINGS

NOT FOR HUMAN USE
KEEP OUT OF REACH OF CHILDREN
FOR ANIMAL USE ONLY
WARNING: This product can expose you to the chemical
aspirin, which is known to the State of California
to cause birth defects or other reproductive harm. For more
information go to www.P65Warnings.ca.gov

Indications:
For use as an aid in reducing fever and for mild analgesia.

Distributed by: MWI

Boise, ID 83705
www.VetOne.net

Made in USA

Take Time - Observe Label Directions

UPC: 313985008701

V1 510016

Lot#:

Exp.:

Rev. 09/18

PACKAGE LABEL

NDC: 13985-300-16

1lb

VETONEAspirin Powder

Apple-Flavored

For animal use only.Keep out of reach of children.

Not for human use.

V1 510016

Net Contents: 1 lb (454g)